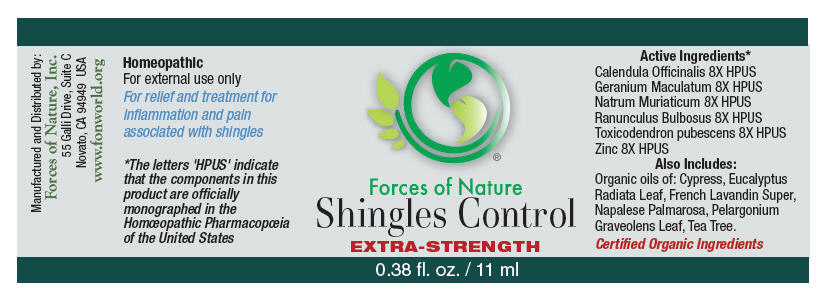 DRUG LABEL: Shingles Control 
NDC: 51393-7223 | Form: SOLUTION/ DROPS
Manufacturer: Forces of Nature
Category: homeopathic | Type: HUMAN OTC DRUG LABEL
Date: 20100824

ACTIVE INGREDIENTS: CALENDULA OFFICINALIS FLOWERING TOP 8 [hp_X]/1000 mL; Geranium Maculatum Root 8 [hp_X]/1000 mL; SODIUM CHLORIDE 8 [hp_X]/1000 mL; Ranunculus bulbosus 8 [hp_X]/1000 mL; Toxicodendron pubescens leaf 8 [hp_X]/1000 mL; Zinc 8 [hp_X]/1000 mL

Shingles Control Extra Strength

Drug Facts

Indications

For the temporary relief of inflammation, itching and redness associated with shingles.

ACTIVE INGREDIENT

PURPOSE

Homeopathic Active Ingredients [The letters 'HPUS' indicate that the components in this product are officially monographed in the Homœopathic Pharmacopœia of the United States.]
Equal parts of: | Purpose
Calendula Officinalis 8X HPUS | Promotes healthy skin
Geranium Maculatuum 8X HPUS | Healing for ulcers in skin
Natrum Muriaticum 8X HPUS | Remedy for herpes, skin eruptions, hives
Ranunculus Bulbosus 8X HPUS | Remedy for herpes, shingles, burning, itching
Toxicodendron Pubescens 8X | Remedy for eruptions of shingles
Zinc 8X | Support for immune function

Also Contains Certified Organic

Cypress Oil, Eucalptus Radiata Oil, Lavandin Oil, Palmarosa Oil, Pelargonium Graveolens Leaf Oil, Tea Tree Oil

Directions

Apply to area of outbreak. For best results apply immediately at the first sign of an outbreak. Apply 3-5 times per day during an outbreak or when you feel one coming on. Use of this product during the prodrome phase (tingling before the outbreak that some people experience) improves results. It may also be helpful to rub this oil on the soles of your feet 3 times per day during an outbreak.

For external use only. Avoid contact with eyes.

Warnings

ASK DOCTOR

If symptoms of pain and swelling worsen consult a health care professional. Some individuals may be sensitive to tea tree or other oils. Begin with a small drop to determine if the product causes any increased redness or irritation and discontinue use if it irritates your skin.

PREGNANCY OR BREAST FEEDING

If you are pregnant or breast-feeding, ask a health professional before use.

KEEP OUT OF REACH OF CHILDREN

Keep out of the reach of children. If accidental ingestion, get medical help or contact a Poison Control Center.

STOP USE

For external use only. Do not apply to the eyes or mucous membranes. Keep all medicines out of the reach of children. Stop use and ask a doctor if condition worsens or symptoms last more than 7 days.

Manufactured by:
Forces of Nature, Inc
55 Galli Drive, Suite C
Novato, CA 94949 USA
www.fonworld.org

Product questions?

877-975-3797

NDC #: 51393-7223-1 (11ml) // 51393-7223-2 (33ml)

PRINCIPAL DISPLAY PANEL - 11 ml Bottle Label

Forces of Nature

Shingles Control
EXTRA-STRENGTH

0.38 fl. oz. / 11 ml